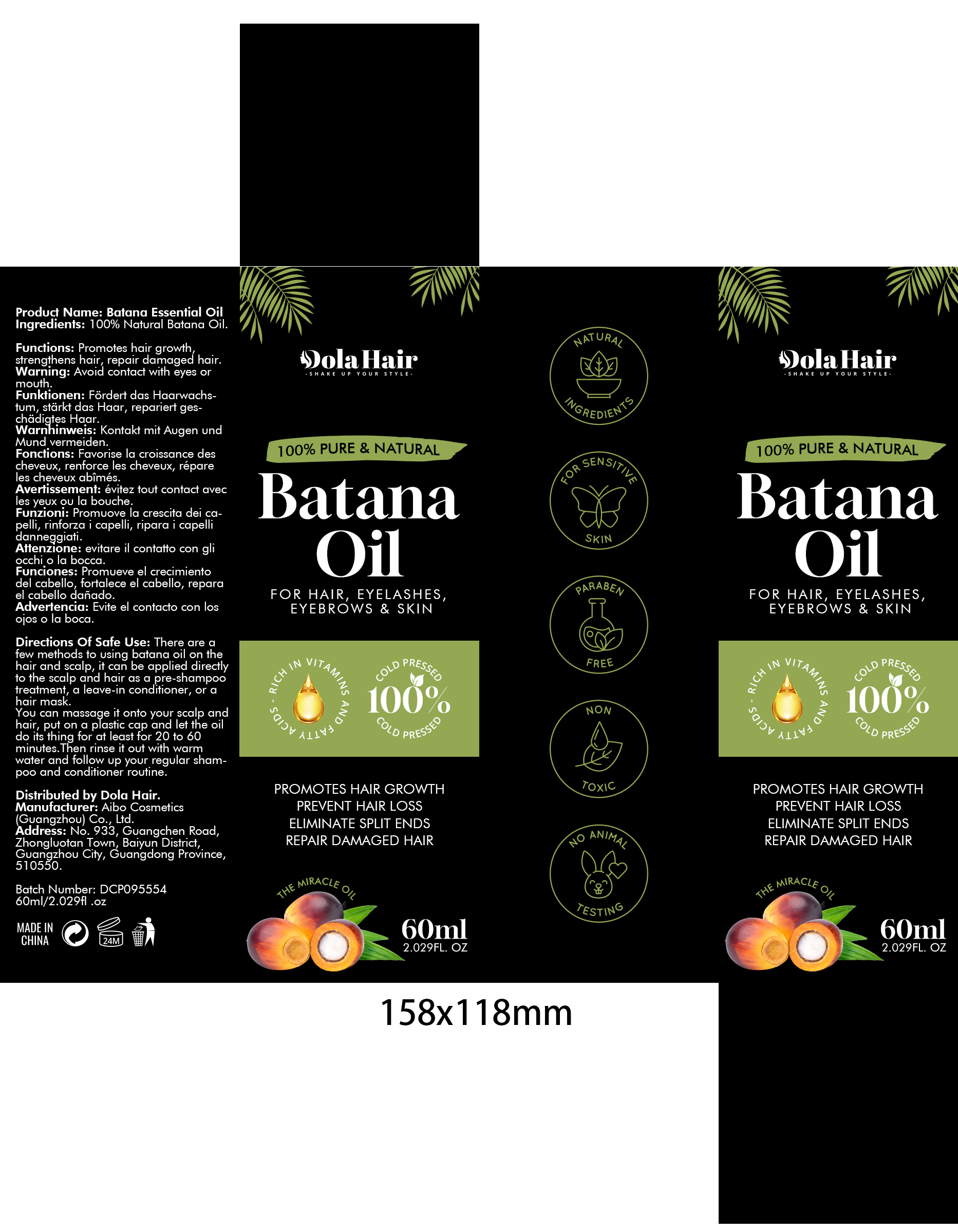 DRUG LABEL: Batana Essential Oil
NDC: 84372-016 | Form: LIQUID
Manufacturer: Shenzhen Zhumeng Times Technology Co., Ltd.
Category: otc | Type: HUMAN OTC DRUG LABEL
Date: 20240821

ACTIVE INGREDIENTS: DAVANA OIL 100 g/100 mL
INACTIVE INGREDIENTS: WATER

Active ingredients

Naturdl Batana Oil 100%

Purpose

Hair growth, strengthens hair, repairs damaged hair

Uses

Apply directly to scalp and hair as pre-shampoo treatment; massage into scalp and leave in for 20-60 minutes before rinsing out with warm water and shampoo/conditioner routine

Warnings

Avoid contact with eyes or mouth

Dosage and administration

For external use only.

Do not use

Stop use and ask a doctor if

chest pain, rapid heartbeat, faintness, or dizziness occurs

sudden, unexplained weight gain occurs

your hands or feet swell

scalp irritation or redness occurs

unwanted facial hair growth occurs

you do not see hair regrowth in 4 months

May be harmful if used when pregnant or breast-feeding.

Keep out of reach of children, lf swallowed, get medical help or contact a Poison Control Center right away.

When using section

do not apply on other parts of the body

avoid contact with the eyes. in case of accidental contact, rinse eyes with large amounts of cool tap water

some people have experienced changes in hair color and/or texture

it takes time to regrow hair. Results may occur at 2 months with twice a day usage. For some people, you may need to use this product for at least 4 months before you see results.

the amount of hair regrowth is different for each person. This product will notwork for all men.

Keep out of reach of children.

If sxralowed, get medical help or contact a Poison Conirol Cenler ngiht away.

stop use

on broken or irritated scalp

Inactive ingredients

Water